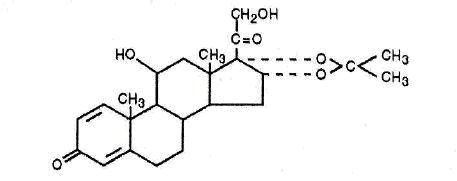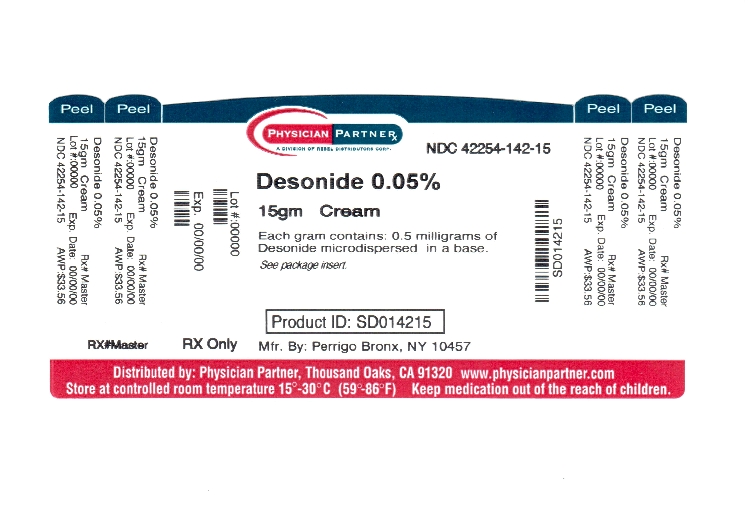 DRUG LABEL: Desonide
NDC: 42254-142 | Form: CREAM
Manufacturer: Rebel Distributors Corp
Category: prescription | Type: HUMAN PRESCRIPTION DRUG LABEL
Date: 20120124

ACTIVE INGREDIENTS: DESONIDE 0.5 mg/1 g
INACTIVE INGREDIENTS: ALUMINUM SULFATE; CALCIUM ACETATE; CETOSTEARYL ALCOHOL; ICODEXTRIN; GLYCERIN; LIGHT MINERAL OIL; WATER; SODIUM LAURYL SULFATE; PETROLATUM

Desonide Cream, 0.05%

For Dermatologic Use Only

Not for Ophthalmic Use

Rx Only

DESCRIPTION

Desonide Cream, 0.05% contains desonide (Pregna-1,4-diene-3,20-dione,11,21-dihydroxy-16,17-[(1-methylethylidene)bis(oxy)]-,(11β,16α)) a synthetic corticosteroid for topical dermatologic use. The corticosteroids constitute a class of primary synthetic steroids used topically as anti-inflammatory and antipruritic agents.

Chemically, desonide, the active ingredient in Desonide Cream, 0.05% is C24H32O6. It has the following structural formula:

The molecular weight of desonide is 416.51. It is a white to off-white powder. The solubility of desonide in distilled water saturated with ether is 184 mg/L.

Each gram of Desonide Cream, 0.05% contains 0.5 milligram of desonide microdispersed in a base of aluminum sulfate, calcium acetate, cetyl stearyl alcohol, dextrin, glycerin, light mineral oil, purified water, sodium lauryl sulfate, synthetic beeswax, and white petrolatum. Desonide Cream, 0.05% is preserved with methylparaben and buffered to pH 4.2 - 5.0.

CLINICAL PHARMACOLOGY

Like other topical corticosteroids, desonide has anti-inflammatory, antipruritic, and vasoconstrictive properties. The mechanism of the anti-inflammatory activity of the topical steroids, in general, is unclear. However corticosteroids are thought to act by the induction of phospholipase A2 inhibitory proteins, collectively called lipocortins. It is postulated that these proteins control the biosynthesis of potent mediators of inflammation such as prostaglandins and leukotrienes by inhibiting the release of their common precursor arachidonic acid. Arachidonic acid is released from membrane phospholipids by phospholipase A2.

Pharmacokinetics

The extent of percutaneous absorption of topical corticosteroids is determined by many factors, including the vehicle and the integrity of the epidermal barrier. Occlusive dressings with hydrocortisone for up to 24 hours have not been demonstrated to increase penetration; however, occlusion of hydrocortisone for 96 hours markedly enhances penetration. Topical corticosteroids can be absorbed from normal intact skin. Inflammation and/or other disease processes in the skin may increase percutaneous absorption.

Studies performed with Desonide Cream, 0.05% indicate that it is in the low range of potency as compared with other topical corticosteroids.

INDICATIONS AND USAGE

Desonide Cream, 0.05% is a low potency corticosteroid indicated for the relief of the inflammatory and pruritic manifestations of corticosteroid responsive dermatoses.

It should not be used for longer than two weeks unless directed by a physician.

CONTRAINDICATIONS

Desonide Cream, 0.05% is contraindicated in those patients with a history of hypersensitivity to any of the components of the preparation.

PRECAUTIONS

General

Systemic absorption of topical corticosteroids can produce reversible hypothalamic-pituitary-adrenal (HPA) axis suppression with the potential for glucocorticosteroid insufficiency after withdrawal of treatment. Manifestations of Cushing's syndrome, hyperglycemia, and glucosuria can also be produced in some patients by systemic absorption of topical corticosteroids while on treatment.

Patients applying a topical steroid to a large surface area or to areas under occlusion should be evaluated periodically for evidence of HPA axis suppression. This may be done by using the ACTH stimulation, A.M. plasma cortisol, and urinary free cortisol tests. Patients receiving superpotent corticosteroids should not be treated for more than two weeks at a time and only small areas should be treated at any one time due to the increased risk of HPA suppressions.

One of ten patients treated for one week under occlusion (30% of body surface) with Desonide Cream, 0.05% developed HPA axis suppression as determined by metapyrone testing.

If HPA axis suppression is noted, an attempt should be made to withdraw the drug, to reduce the frequency of application, or to substitute a less potent corticosteroid. Recovery of HPA axis function is generally prompt upon discontinuation of topical corticosteroids. Infrequently, signs and symptoms of glucocorticosteroid insufficiency may occur requiring supplemental systemic corticosteroids. For information on systemic supplementation, see prescribing information for those products.

Pediatric patients may be more susceptible to systemic toxicity from equivalent doses due to their larger skin surface to body mass ratios (see PRECAUTIONS - Pediatric Use).

If irritation develops, Desonide Cream, 0.05% should be discontinued and appropriate therapy instituted. Allergic contact dermatitis with corticosteroids is usually diagnosed by observing a failure to heal rather than noting a clinical exacerbation as with most topical products not containing corticosteroids. Such an observation should be corroborated with appropriate diagnostic patch testing.

If concomitant skin infections are present or develop, an appropriate antifungal or antibacterial agent should be used. If a favorable response does not occur promptly, use of Desonide Cream, 0.05% should be discontinued until the infection has been adequately controlled.

Desonide Cream, 0.05% should not be used in the presence of infection at the treatment site, hypersensitivity to corticosteroids, or pre-existing skin atrophy.

Desonide Cream, 0.05% should not be used in the eyes.

FOR EXTERNAL USE ONLY.

Information for Patients

Patients using topical corticosteroids should receive the following information and instructions:

1. This medication is to be used as directed by the physician. It is for external use only. Avoid contact with the eyes.
2. This medication should not be used for any disorder other than that for which it was prescribed.
3. The treated skin area should not be bandaged, otherwise covered or wrapped, so as to be occlusive unless directed by the physician.
4. Patients should report to their physician any signs of local adverse reactions.

Laboratory Tests

The following tests may be helpful in evaluating patients for HPA axis suppression:

ACTH stimulation test
A.M. plasma cortisol test
Urinary free cortisol test

Carcinogenesis, Mutagenesis, Impairment of Fertility

Long-term animal studies have not been performed to evaluate the carcinogenic, mutagenic, or fertility impairment potential of Desonide Cream, 0.05%.

Pregnancy

Teratogenic Effects

Pregnancy category C

Corticosteroids have been shown to be teratogenic in laboratory animals when administered systemically at relatively low dosage levels. Some corticosteroids have been shown to be teratogenic after dermal application in laboratory animals. Animal reproductive studies have not been conducted with Desonide Cream, 0.05%. It is also not known whether Desonide Cream, 0.05% can cause fetal harm when administered to a pregnant woman or can affect reproduction capacity. There are no adequate and well-controlled studies in pregnant women. Desonide Cream, 0.05% should be used during pregnancy only if the potential benefit justifies the potential risk to the fetus.

Nursing Mothers

Systemically administered corticosteroids appear in human milk and could suppress growth, interfere with endogenous corticosteroid production, or cause other untoward effects. It is not known whether topical administration of corticosteroids could result in sufficient systemic absorption to produce detectable quantities in human milk. Because many drugs are excreted in human milk, caution should be exercised when Desonide Cream, 0.05% is administered to a nursing woman.

Pediatric Use

Safety and effectiveness in pediatric patients have not been established. Because of a higher ratio of skin surface area to body mass, pediatric patients are at a greater risk than adults of HPA axis suppression and Cushing’s syndrome when they are treated with topical corticosteroids. They are therefore also at greater risk of adrenal insufficiency during or after withdrawal of treatment.

Adverse effects including striae have been reported with inappropriate use of topical corticosteroids in infants and children.

HPA axis suppression, Cushing’s syndrome, linear growth retardation, delayed weight gain and intracranial hypertension have been reported in children receiving topical corticosteroids. Manifestations of adrenal suppression in children include low plasma cortisol levels and absence of response to ACTH stimulation. Manifestations of intracranial hypertension include bulging fontanelles, headaches, and bilateral papilledema.

ADVERSE REACTIONS

In controlled clinical trials, the total incidence of adverse reactions associated with the use of Desonide Cream, 0.05% was approximately 1%. These adverse reactions were pruritus, pain, folliculitis, rash, peripheral edema, pustular rash, sweating, erythema, irritation, and burning. Laboratory abnormalities were found in 3% of the patients. These were hyperglycemia (2%) and liver function abnormality (1%).

The following additional local adverse reactions have been reported infrequently with topical corticosteroids, and they may occur more frequently with the use of occlusive dressings and higher potency corticosteroids. These reactions are listed in approximate decreasing order of occurrence: dryness, folliculitis, acneiform eruptions, perioral dermatitis, allergic contact dermatitis, secondary infection, skin atrophy, striae, miliaria, burning and hypopigmentation.

OVERDOSAGE

Topically applied Desonide Cream, 0.05% can be absorbed in sufficient amounts to produce systemic effects (see PRECAUTIONS).

DOSAGE AND ADMINISTRATION

Desonide Cream, 0.05% should be applied to the affected area as a thin film two to four times daily depending on the severity of the condition.

As with other corticosteroids, therapy should be discontinued when control is achieved. If no improvement is seen within two weeks, reassessment of diagnosis may be necessary.

Desonide Cream, 0.05% should not be used with occlusive dressings.

HOW SUPPLIED

Desonide Cream, 0.05% is available as follows:

15 g tube (NDC 42254-142-15)

STORAGE

Store at 20-25°C (68-77°F)[see USP Controlled Room Temperature].

MANUFACTURED BY

PERRIGO

BRONX, NY 10457

DISTRUBUTED BY

PERRIGO®

ALLEGAN, MI 49010

Rev. 08/09

1A700 RC J3

REPACKAGED BY:

REBEL DISTRIBUTORS CORP

THOUSAND OAKS, CA 91320